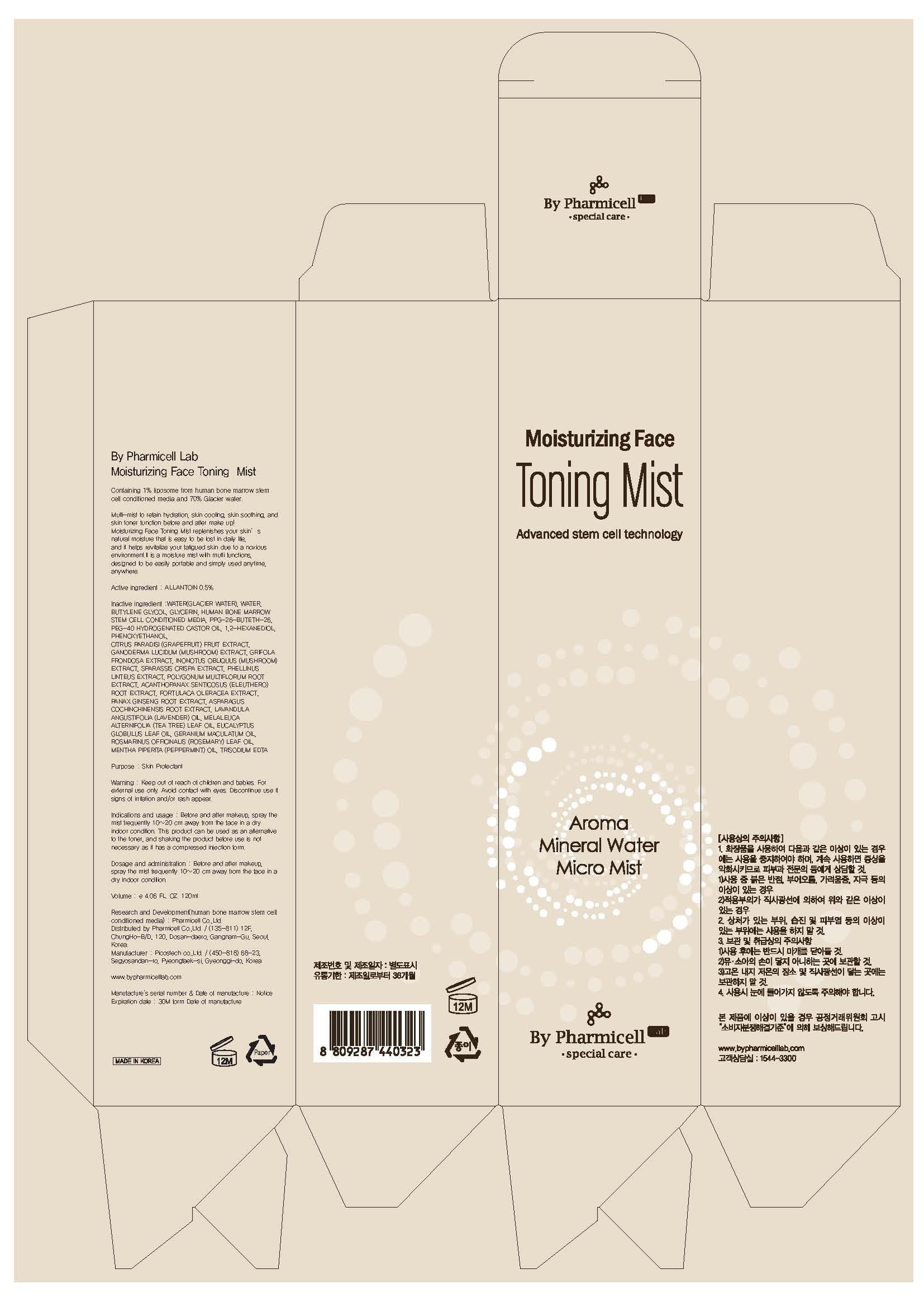 DRUG LABEL: By Pharmicell Lab Moisturizing Face Toning Mist
NDC: 60949-100 | Form: SPRAY
Manufacturer: Pharmicell Co., Ltd.
Category: otc | Type: HUMAN OTC DRUG LABEL
Date: 20130708

ACTIVE INGREDIENTS: ALLANTOIN 0.6 mg/120 mL
INACTIVE INGREDIENTS: WATER; BUTYLENE GLYCOL

ACTIVE INGREDIENT

Active ingredient : ALLANTOIN 0.5%

INACTIVE INGREDIENT

Inactive ingredient : WATER(GLACIER WATER), WATER, BUTYLENE GLYCOL, GLYCERIN, HUMAN BONE MARROW STEM CELL CONDITIONED MEDIA, PPG-26-BUTETH-26, PEG-40 HYDROGENATED CASTOR OIL, 1,2-HEXANEDIOL, PHENOXYETHANOL, CITRUS PARADISI (GRAPEFRUIT) FRUIT EXTRACT, GANODERMA LUCIDUM (MUSHROOM) EXTRACT, GRIFOLA FRONDOSA EXTRACT, INONOTUS OBLIQUUS (MUSHROOM) EXTRACT, SPARASSIS CRISPA EXTRACT, PHELLINUS LINTEUS EXTRACT, POLYGONUM MULTIFLORUM ROOT EXTRACT, ACANTHOPANAX SENTICOSUS (ELEUTHERO) ROOT EXTRACT, PORTULACA OLERACEA EXTRACT, PANAX GINSENG ROOT EXTRACT, ASPARAGUS COCHINCHINENSIS ROOT EXTRACT, LAVANDULA ANGUSTIFOLIA (LAVENDER) OIL, MELALEUCA ALTERNIFOLIA (TEA TREE) LEAF OIL, EUCALYPTUS GLOBULUS LEAF OIL, GERANIUM MACULATUM OIL, ROSMARINUS OFFICINALIS (ROSEMARY) LEAF OIL, MENTHA PIPERITA (PEPPERMINT) OIL, TRISODIUM EDTA

PURPOSE

Purpose : Skin Protectant

WARNINGS

Warning : Keep out of reach of children and babies. For external use only. Avoid contact with eyes. Discontinue use if signs of irritation and/or rash appear.

Keep out of reach of children and babies.

Indications and usage : Before and after makeup, spray the mist frequently 10~20 cm away from the face in a dry indoor condition. This product can be used as an alternative to the toner, and shaking the product before use is not necessary as it has a compressed injection form.

Dosage and administration : Before and after makeup, spray the mist frequently 10~20 cm away from the face in a dry indoor condition.